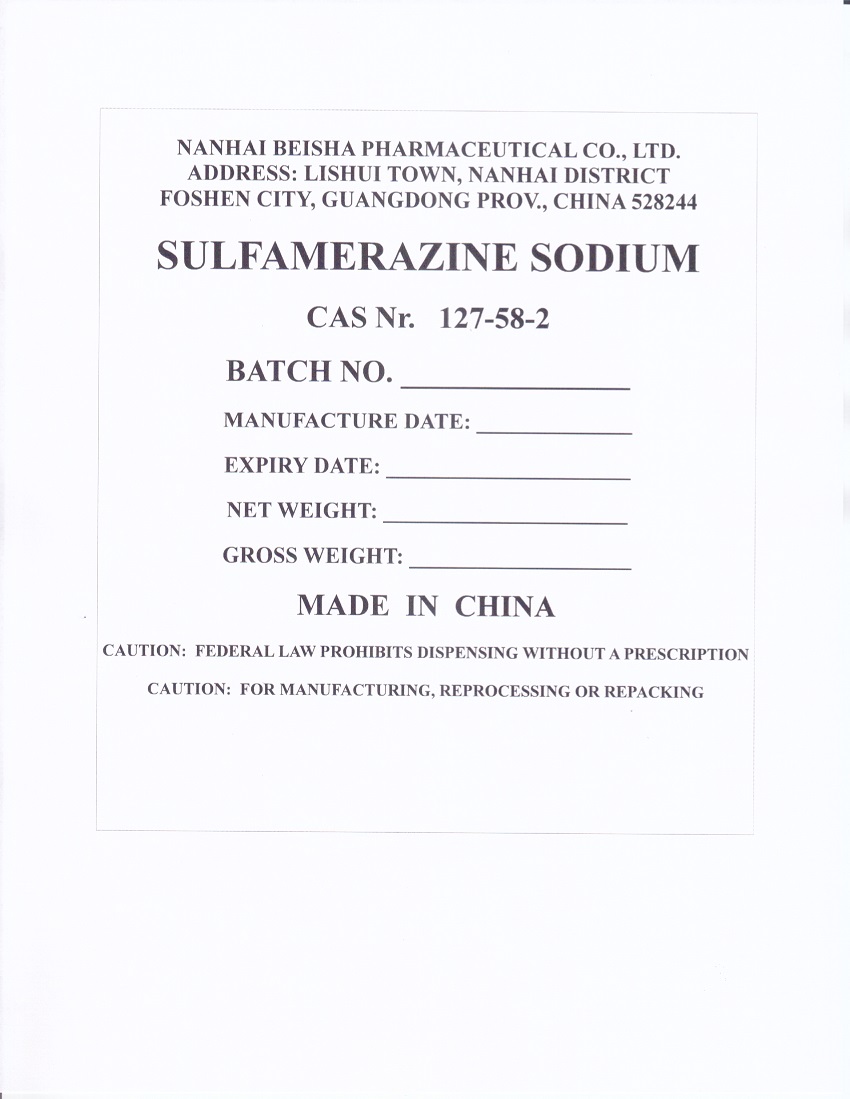 DRUG LABEL: SULFAMERAZINE SODIUM
NDC: 63422-705 | Form: POWDER
Manufacturer: NANHAI BEISHA PHARMACEUTICAL CO., LTD
Category: other | Type: BULK INGREDIENT - ANIMAL DRUG
Date: 20250822

ACTIVE INGREDIENTS: SULFAMERAZINE SODIUM 1 kg/1 kg

PACKAGE LABEL

Add image transcription here...